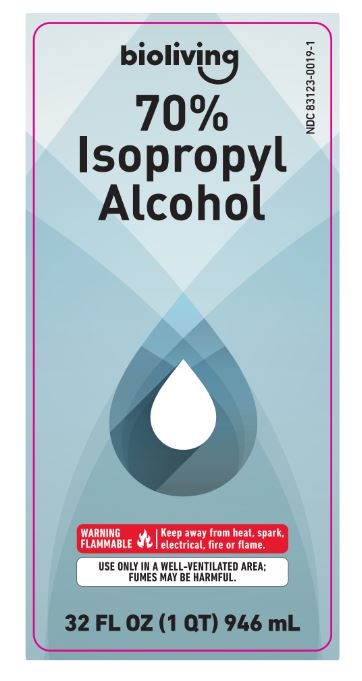 DRUG LABEL: ISOPROPYL ALCOHOL
NDC: 83123-0019 | Form: LIQUID
Manufacturer: BROSANT GROUP LLC
Category: otc | Type: HUMAN OTC DRUG LABEL
Date: 20230117

ACTIVE INGREDIENTS: ISOPROPYL ALCOHOL 70 mL/100 mL
INACTIVE INGREDIENTS: WATER 30 mL/100 mL

Active Ingredient

Isopropyl alcohol (70%conc)

Purpose

First aid antiseptic

Warnings

For external use only.

-if taken internally, serious gastric disturbances will result

Flammable keep away from fire or flamme

-use only in a well-ventilated area; fumes may be toxic

Ask a doctor before use if you have

deep or puncture wounds, animal bites, or serious burns

When using this product

-do not get into eyes

-do not apply over large areas of the body

-do not use longer than one week unless directed by a doctor

Stop use and ask a doctor if

condition persists or gets worse

keep out of reach of children

In case of ingestion, get medical help or contact a Poison Control Center right away (1-800-222-1222)

Directions

-clean affected area

-apply small amount of this product on the area 1-3 times daily

-if bandaged, let dry first

-may be covered with a sterile bandage

Other information

-store at room temperature

-does not contain, nor is intended as a subsitute for grain or ethyl alcohol

Inactive ingredient

purified water

Directions

-clean affected area

-apply small amount of this product on the area 1-3 times daily

-if bandaged, let dry first

-may be covered with a sterile bandage

PACKAGE LABEL

Bioliving

70% isopropyl alcohol

warning flammable

keep away from heat, spark, electrical, fire or flamme

use only in a well-ventilated area; fumes may be harmful

32FL OZ (1QT) 946 mL